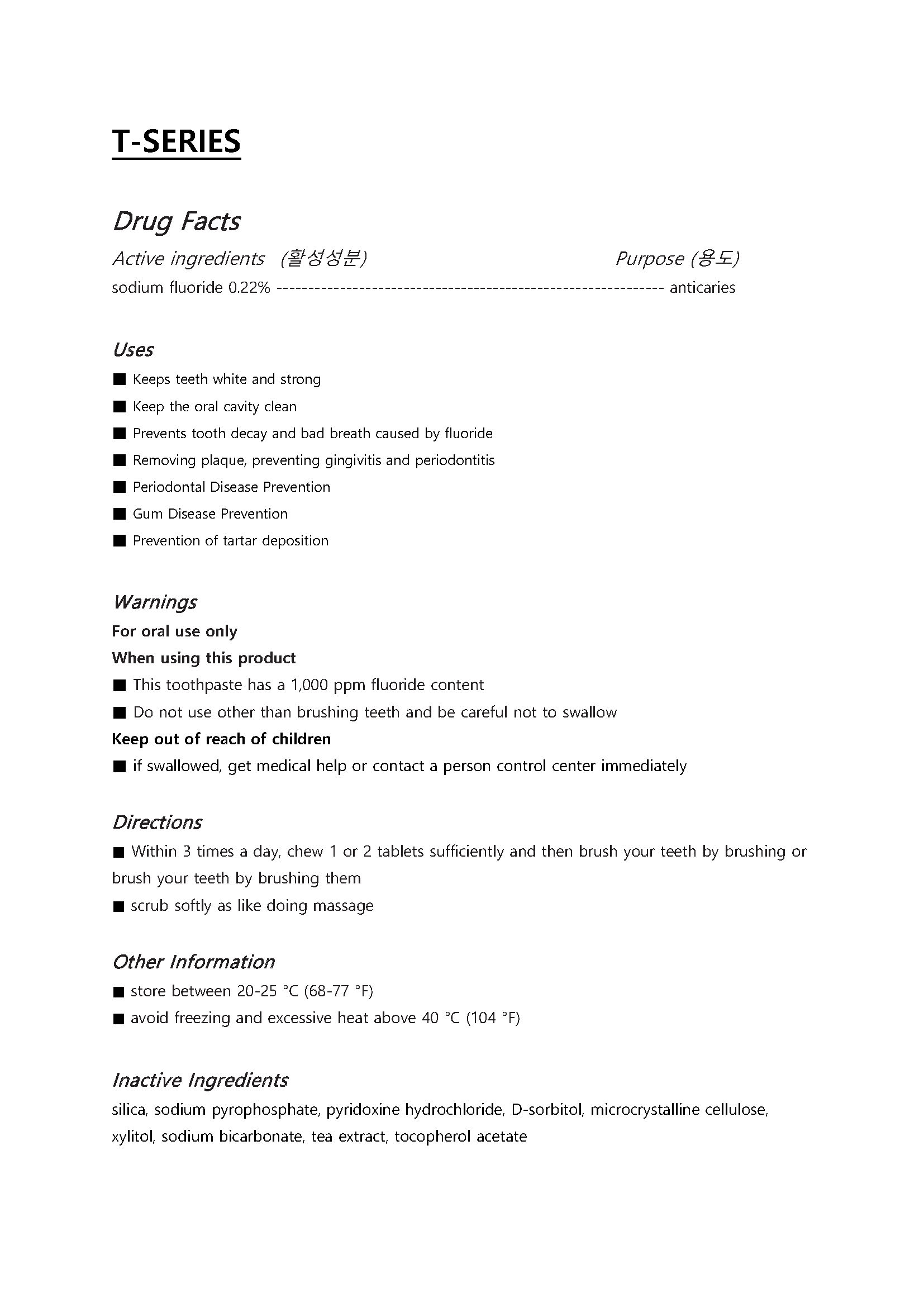 DRUG LABEL: T-SERIES
NDC: 76058-001 | Form: TABLET
Manufacturer: SUNGWON PHARMACEUTICAL CO., LTD.
Category: otc | Type: HUMAN OTC DRUG LABEL
Date: 20191018

ACTIVE INGREDIENTS: SODIUM FLUORIDE 0.22 1/1 1
INACTIVE INGREDIENTS: SODIUM BICARBONATE; SORBITOL

ACTIVE INGREDIENT

sodium fluoride

INACTIVE INGREDIENT

silica, sodium pyrophosphate, pyridoxine hydrochloride, D-sorbitol, microcrystalline cellulose, xylitol, sodium bicarbonate, tea extract, tocopherol acetate, etc

PURPOSE

■ Keeps teeth white and strong

■ Keep the oral cavity clean

■ Prevents tooth decay and bad breath caused by fluoride

■ Removing plaque, preventing gingivitis and periodontitis

■ Periodontal Disease Prevention

■ Gum Disease Prevention

■ Prevention of tartar deposition

KEEP OUT OF REACH OF CHILDREN

WARNING

For oral use only
When using this product

■ This toothpaste has a 1,000 ppm fluoride content

■ Do not use other than brushing teeth and be careful not to swallow

Keep out of reach of children

■ if swallowed, get medical help or contact a person control center immediately

USES

for oral use only

INDICATION & USAGE SECTION

■ Within 3 times a day, chew 1 or 2 tablets sufficiently and then brush your teeth by brushing or brush your teeth by brushing them

■ scrub softly as like doing massage